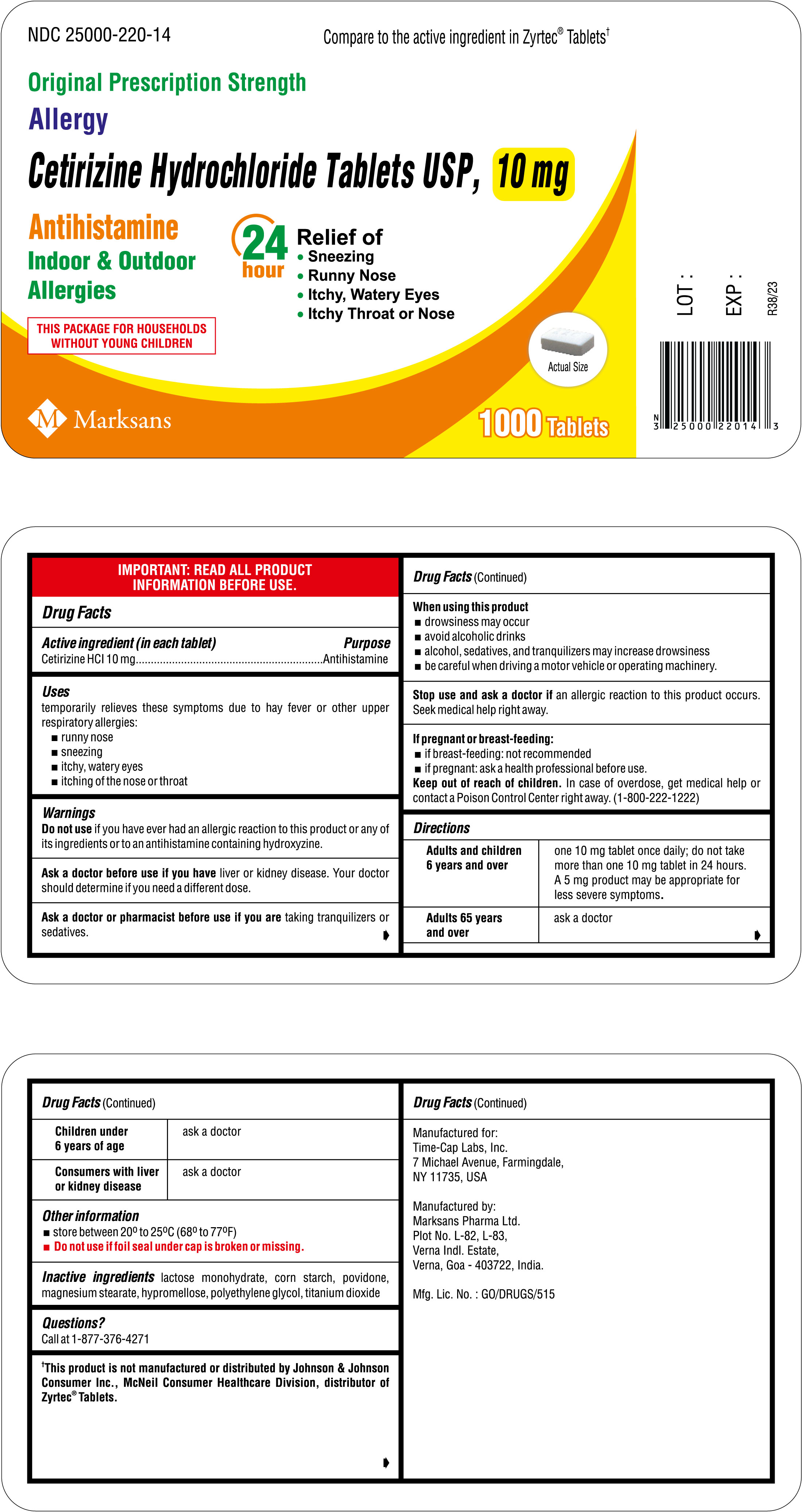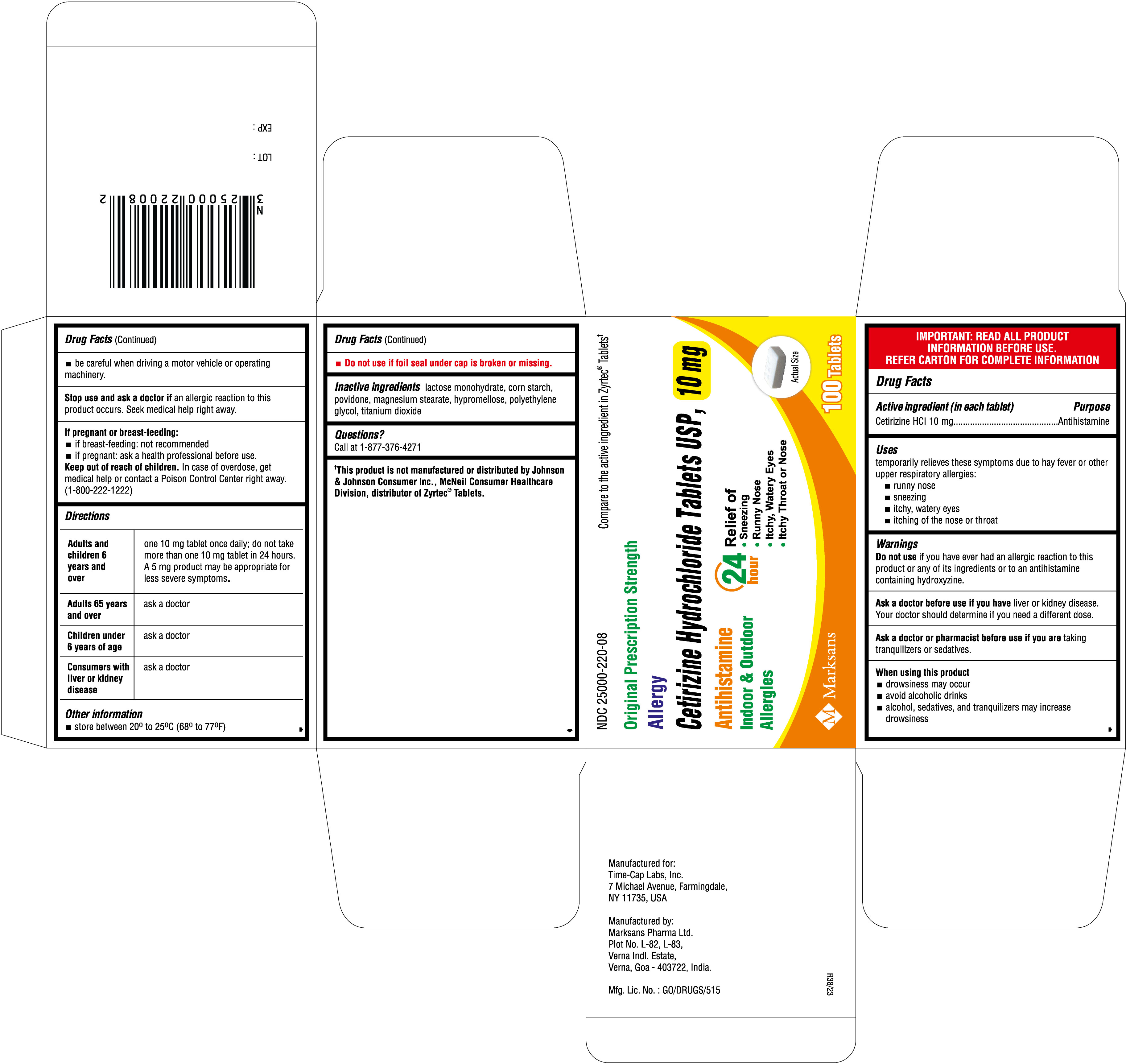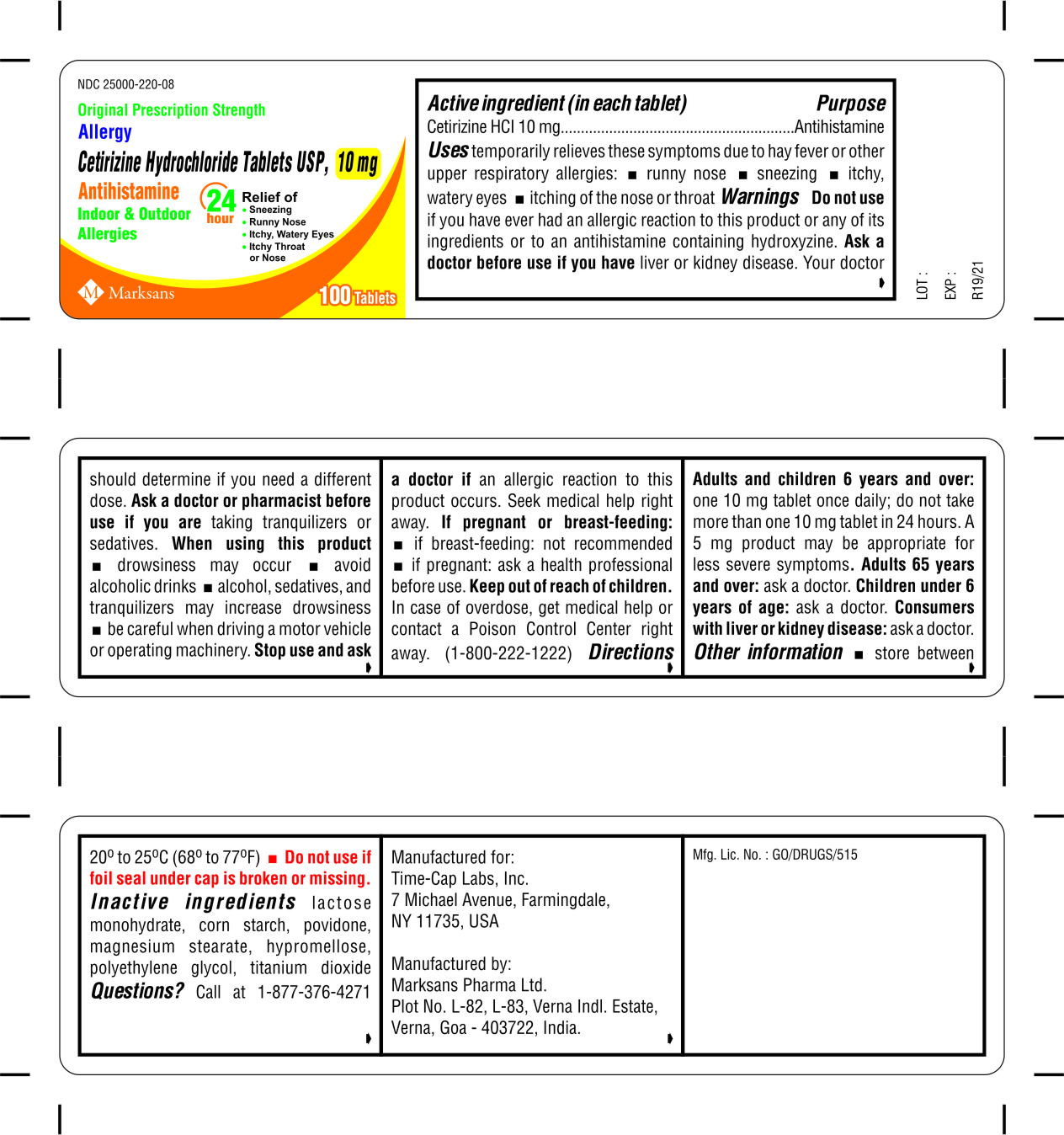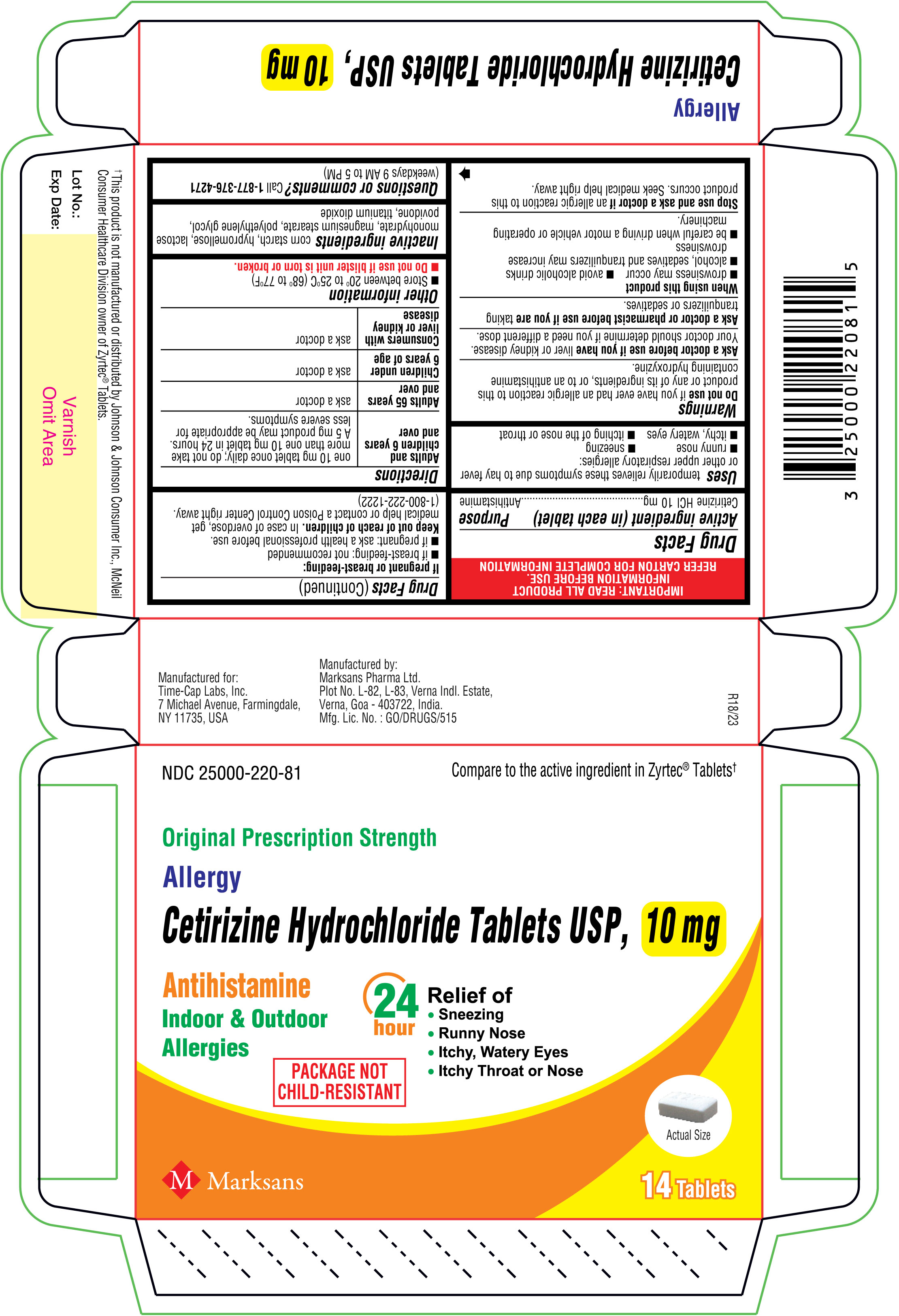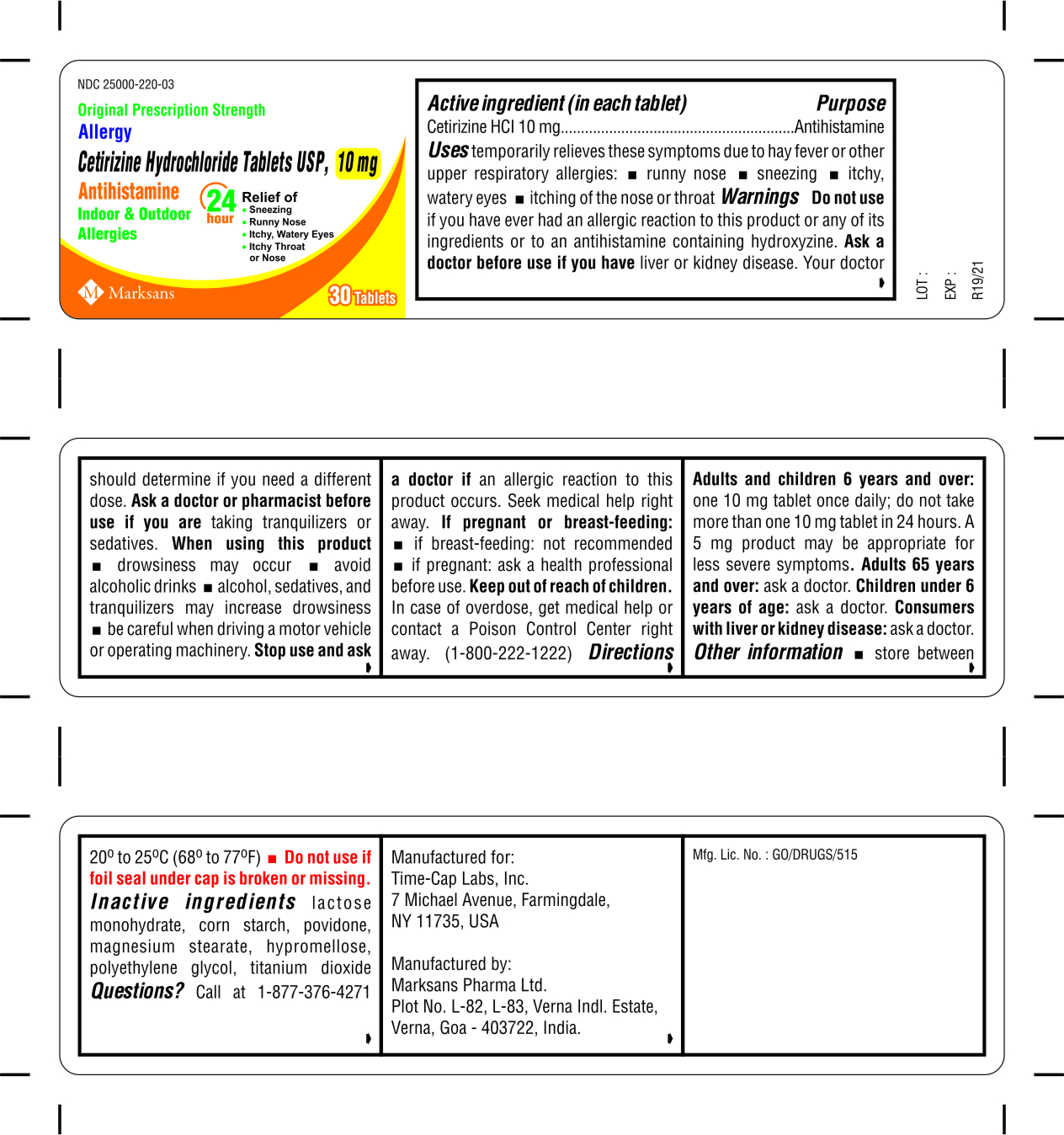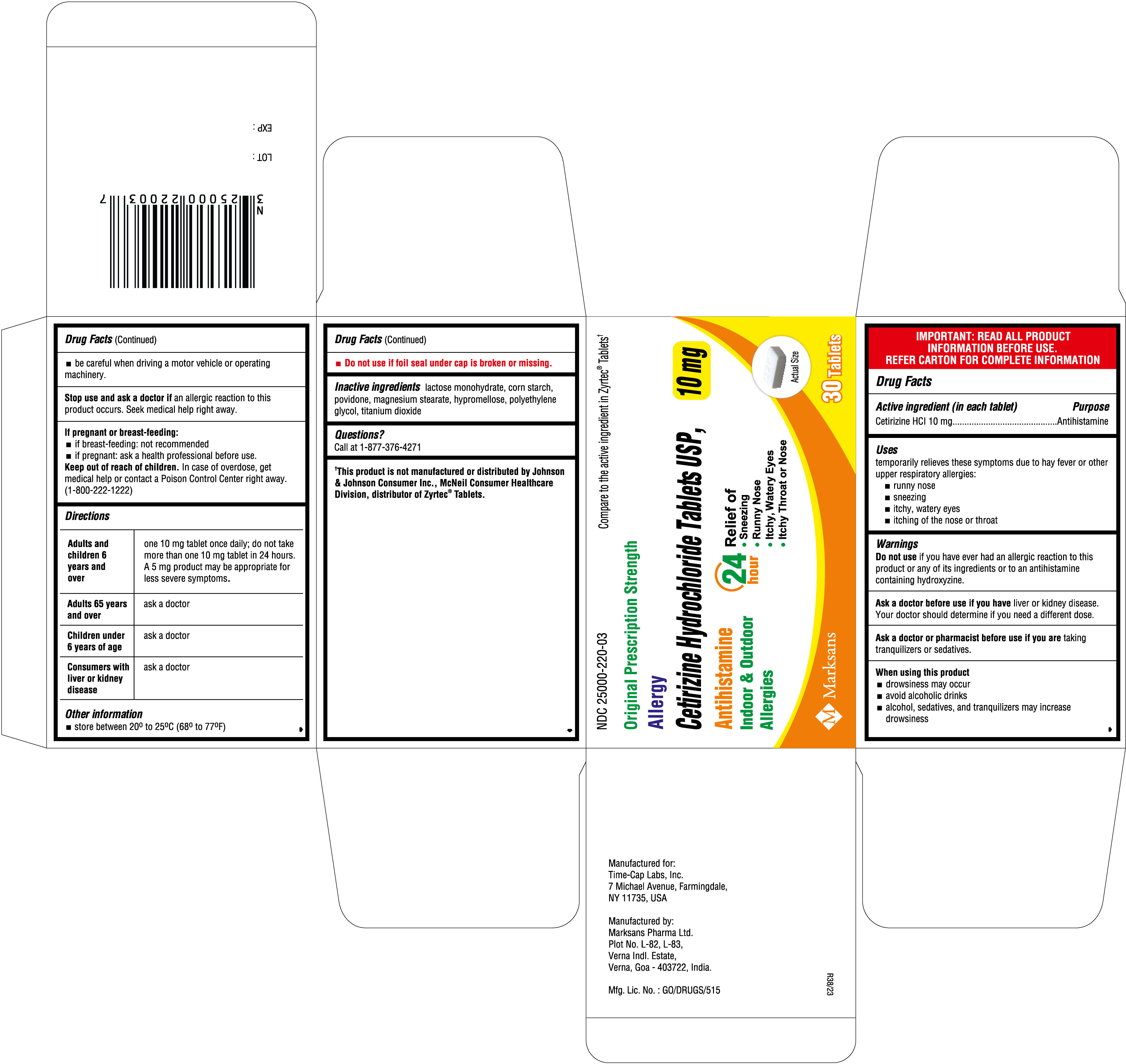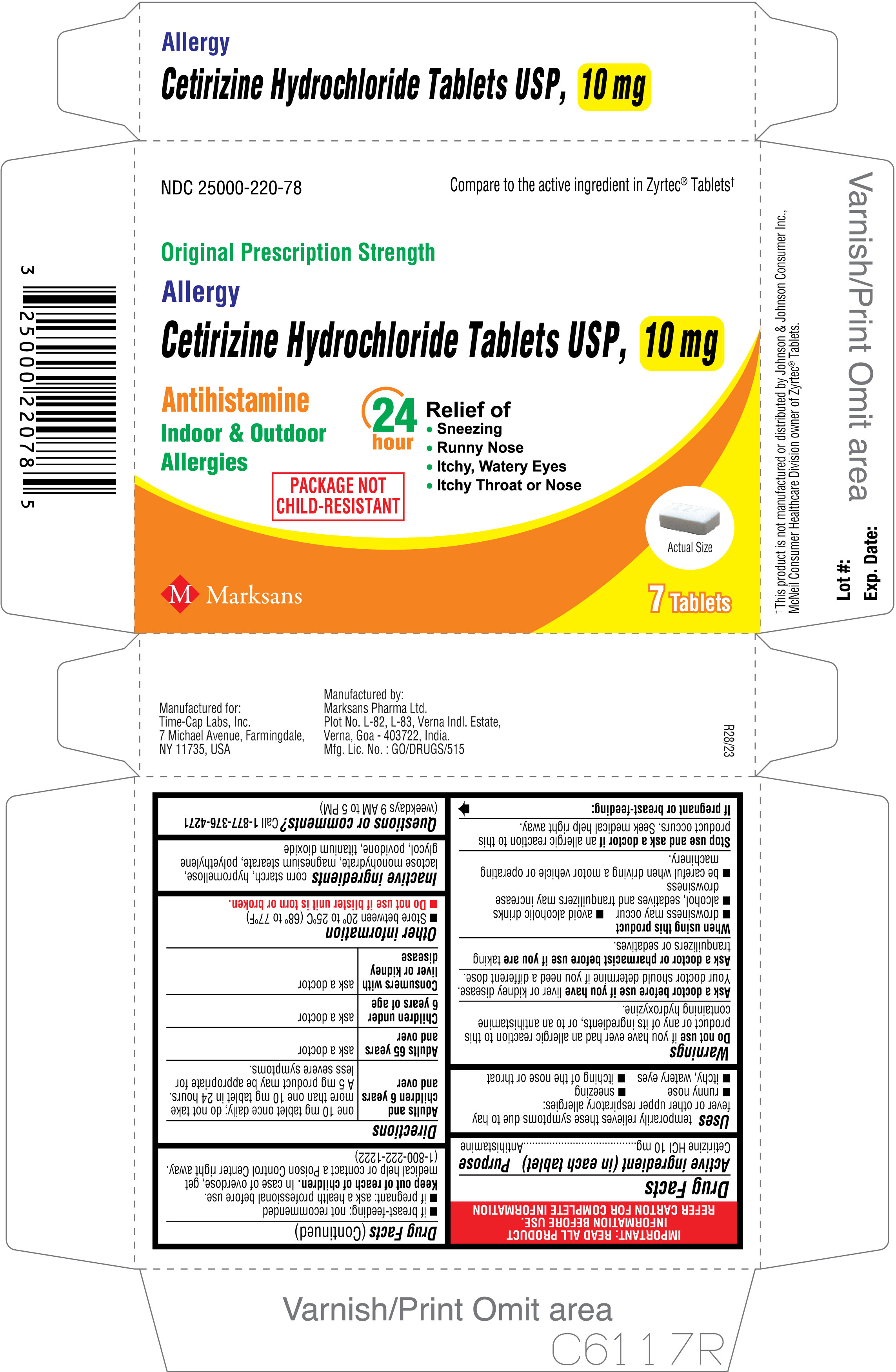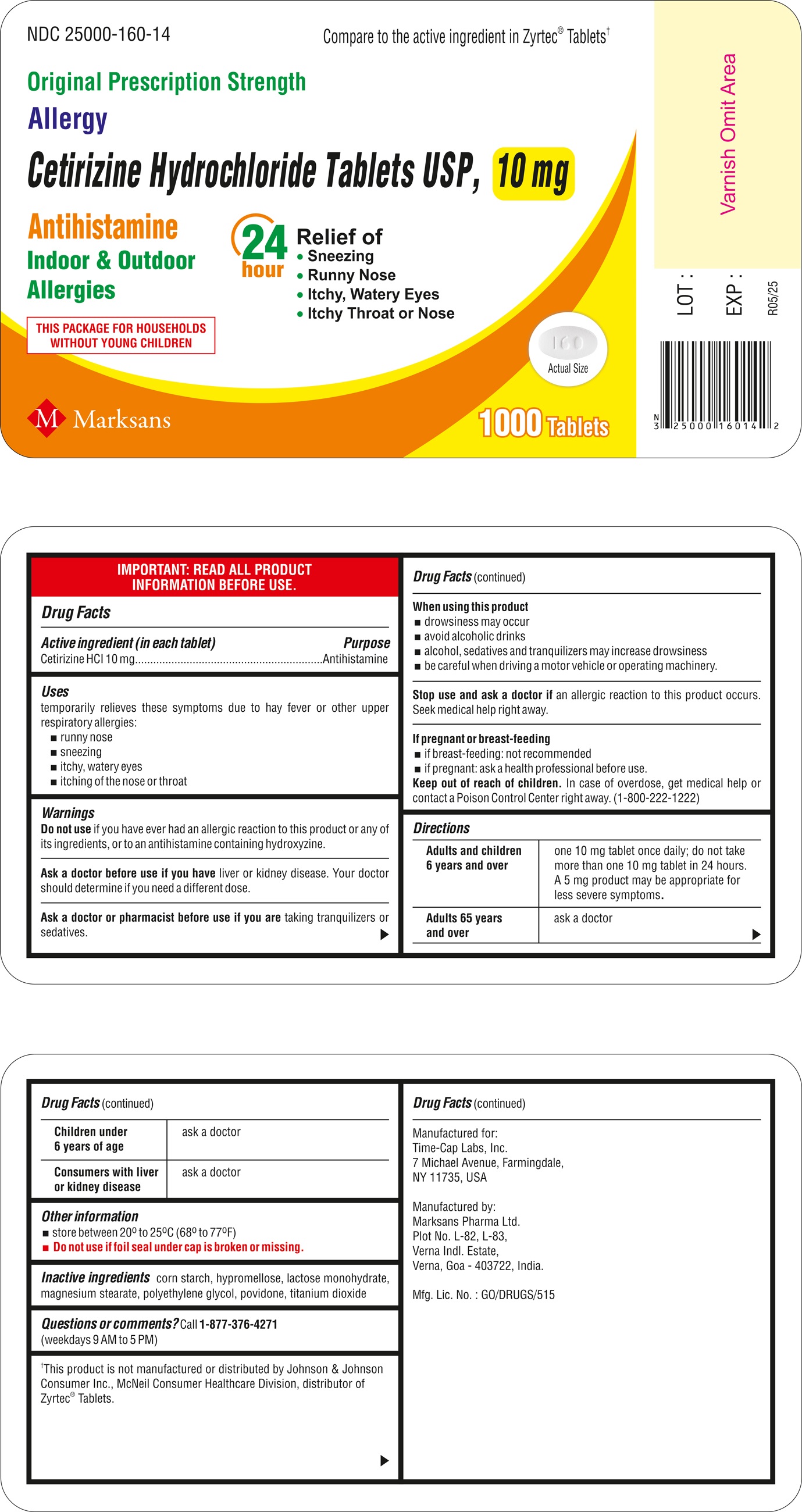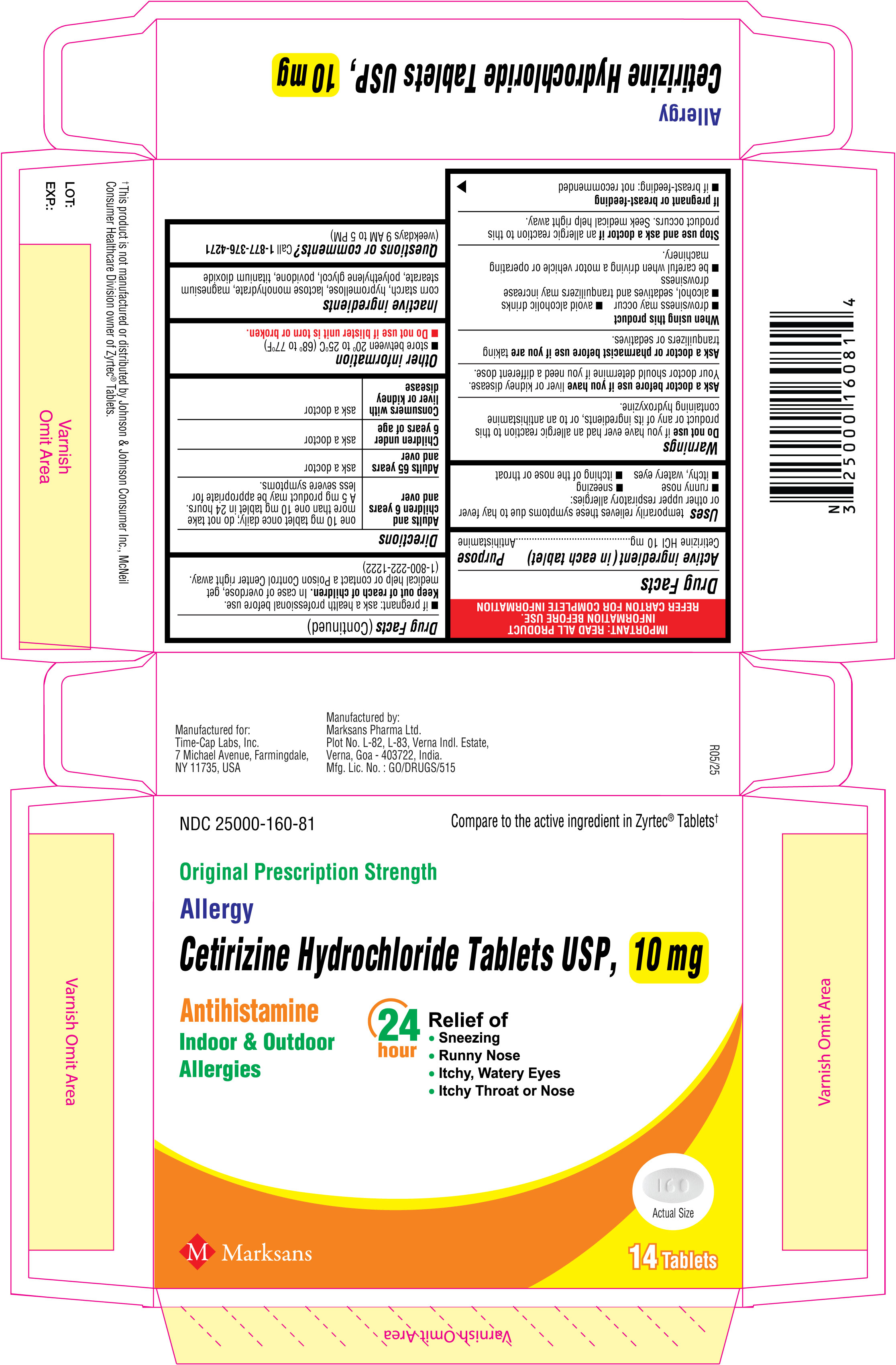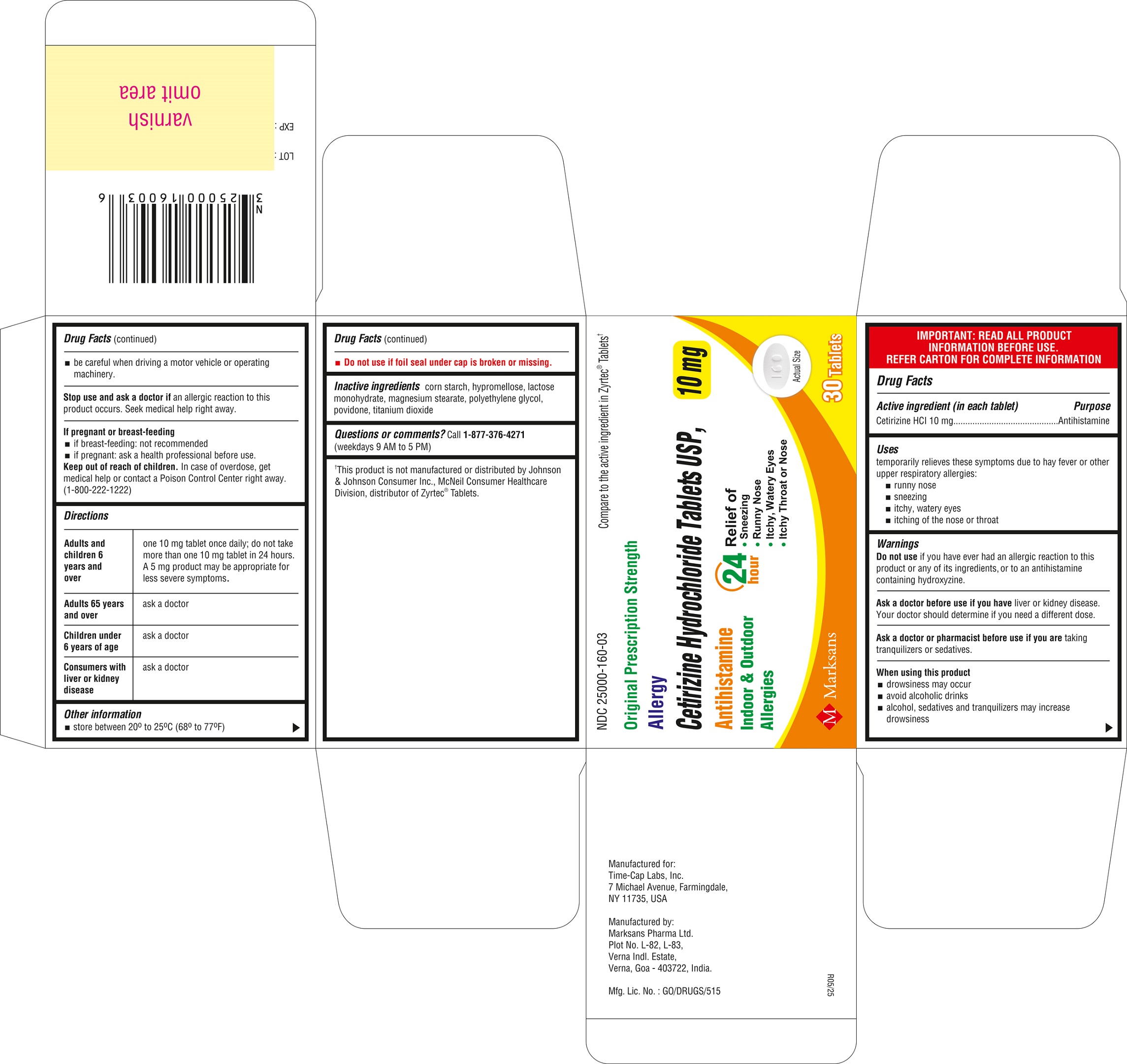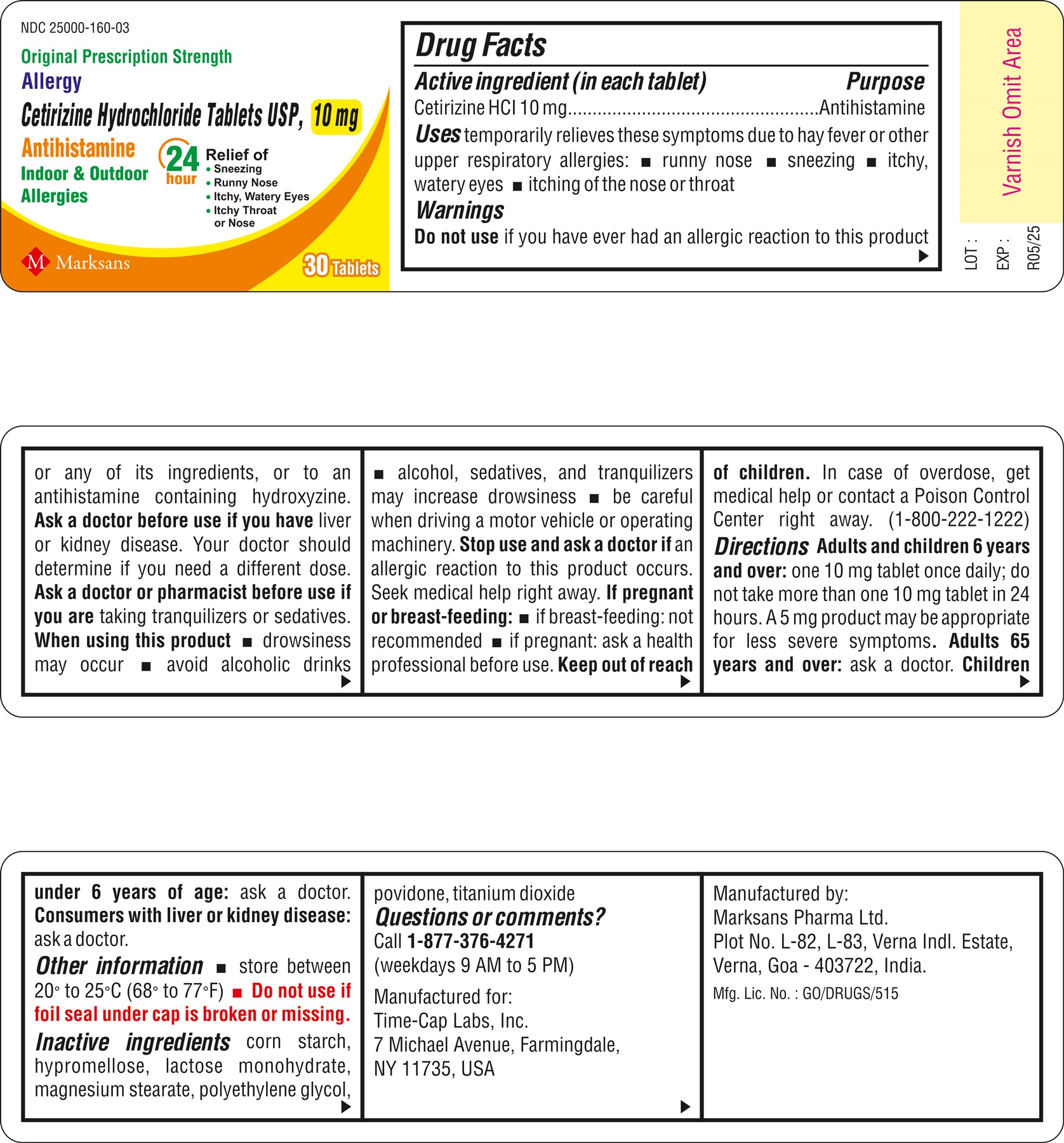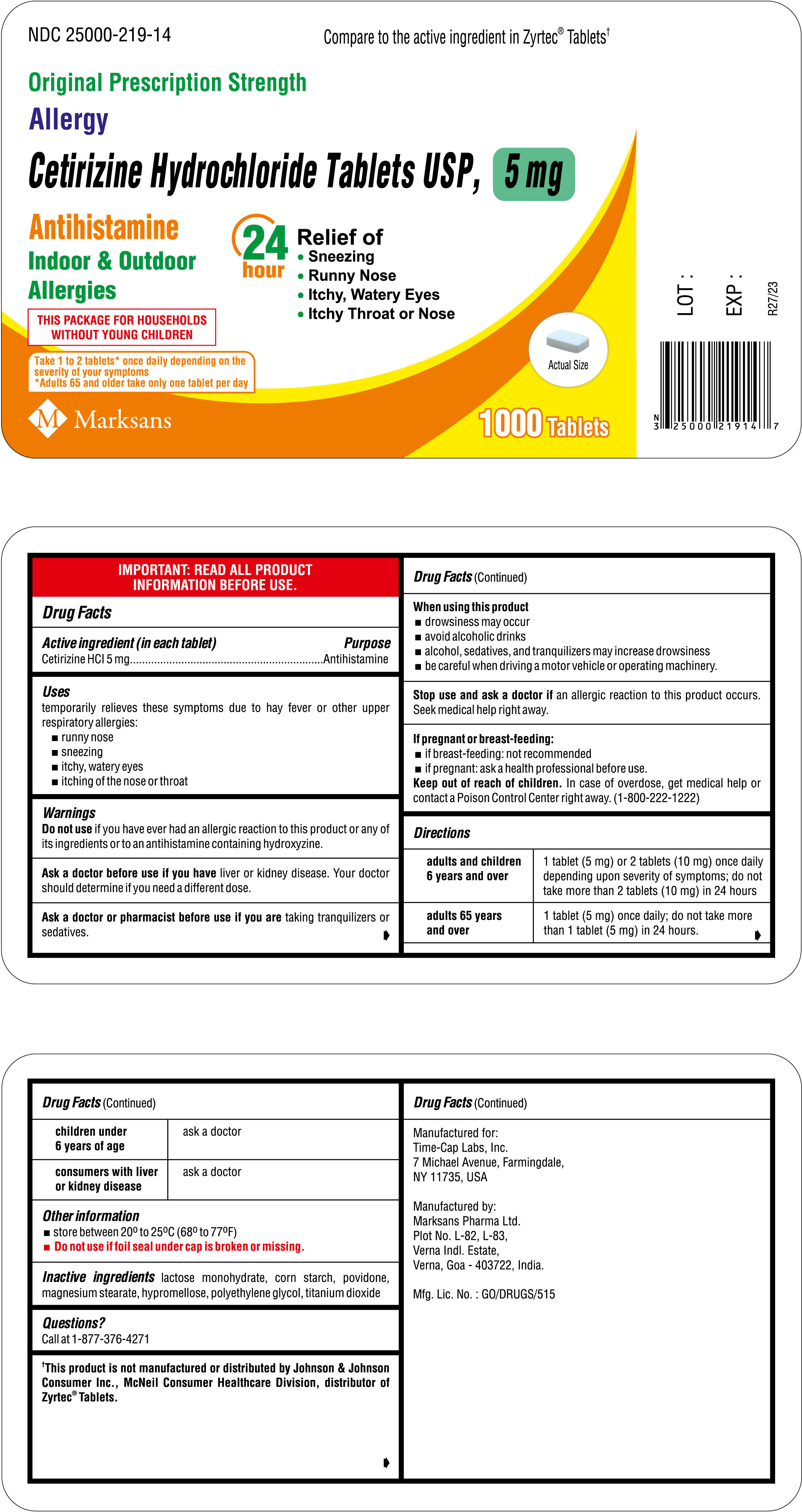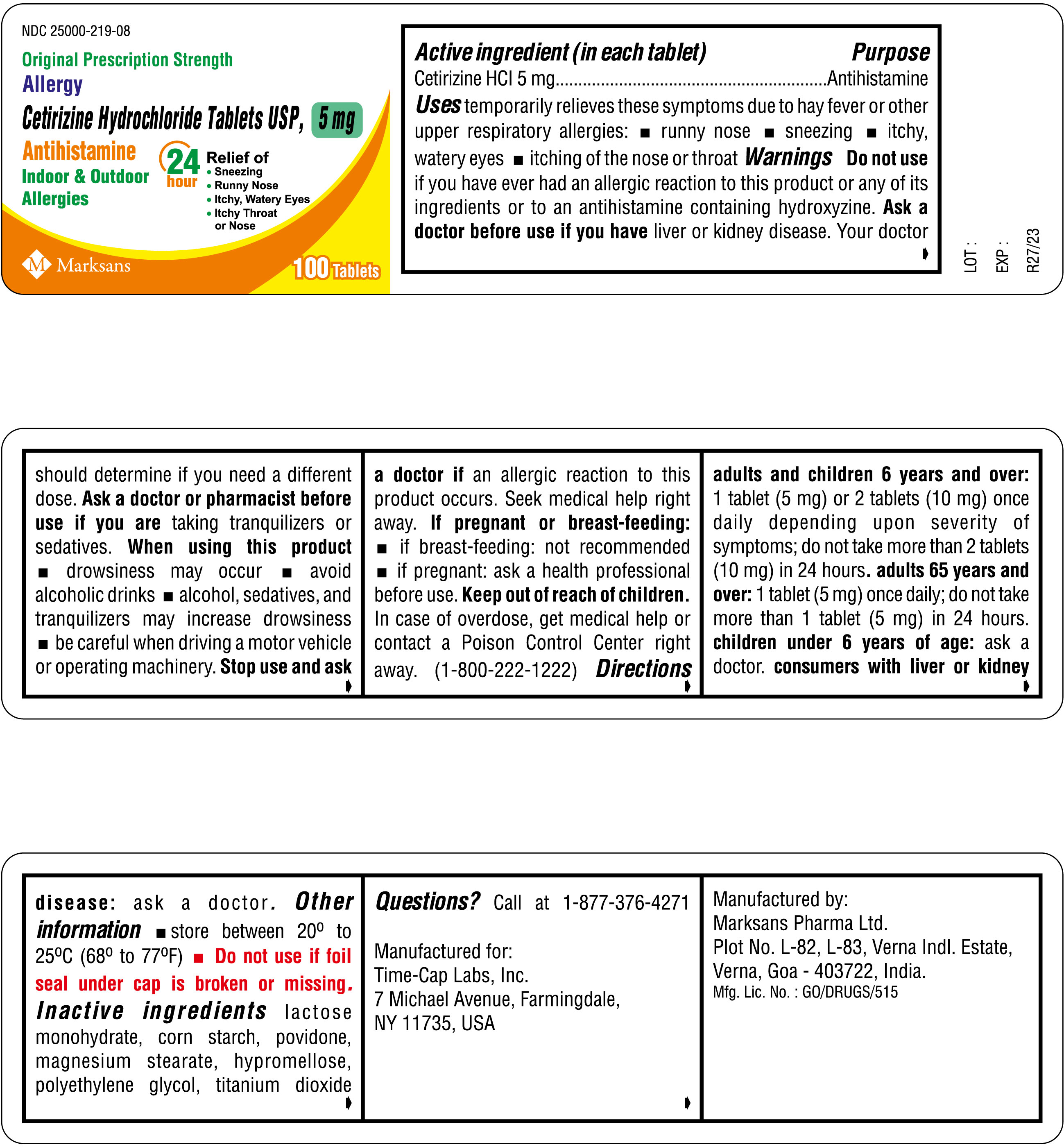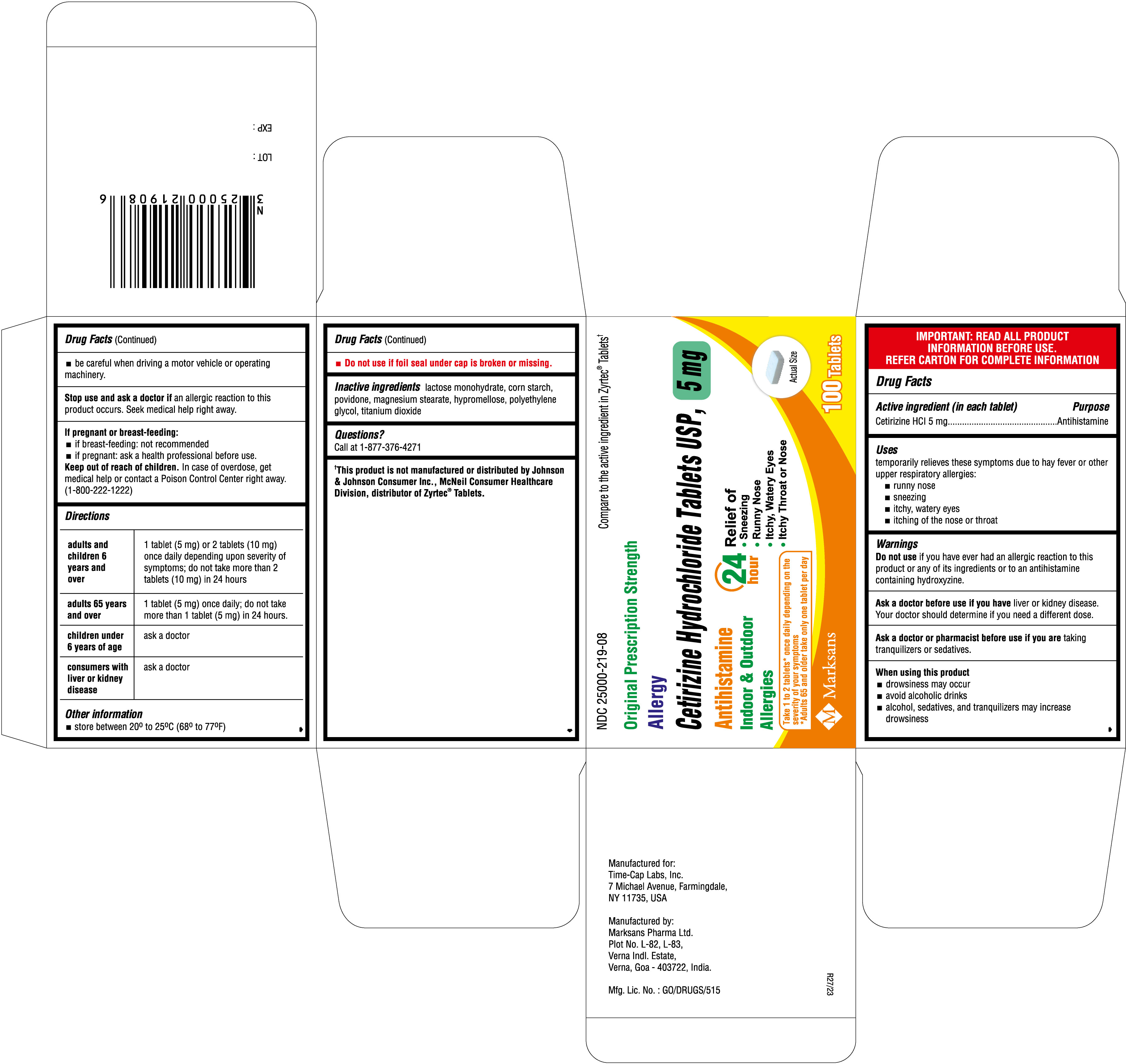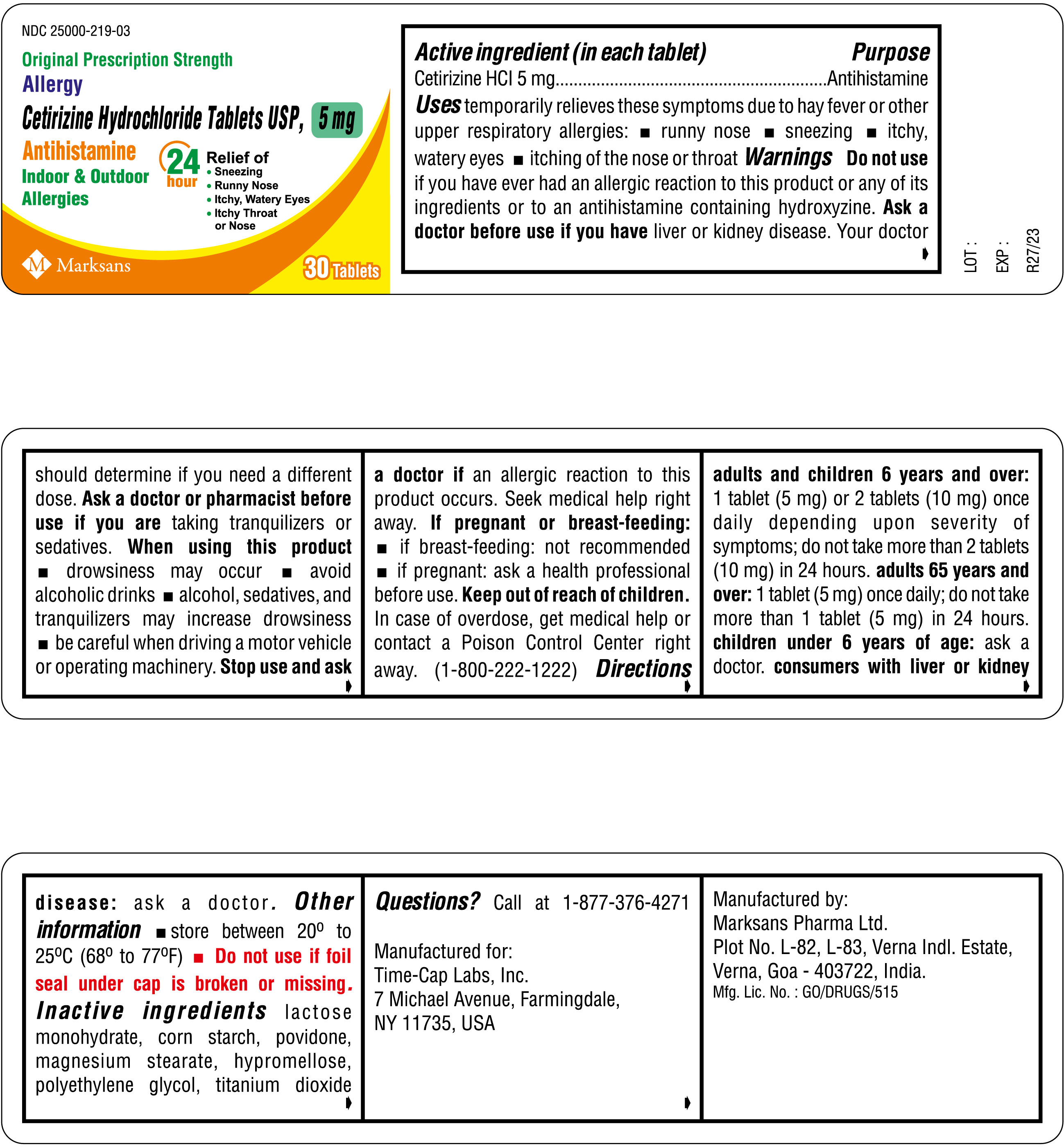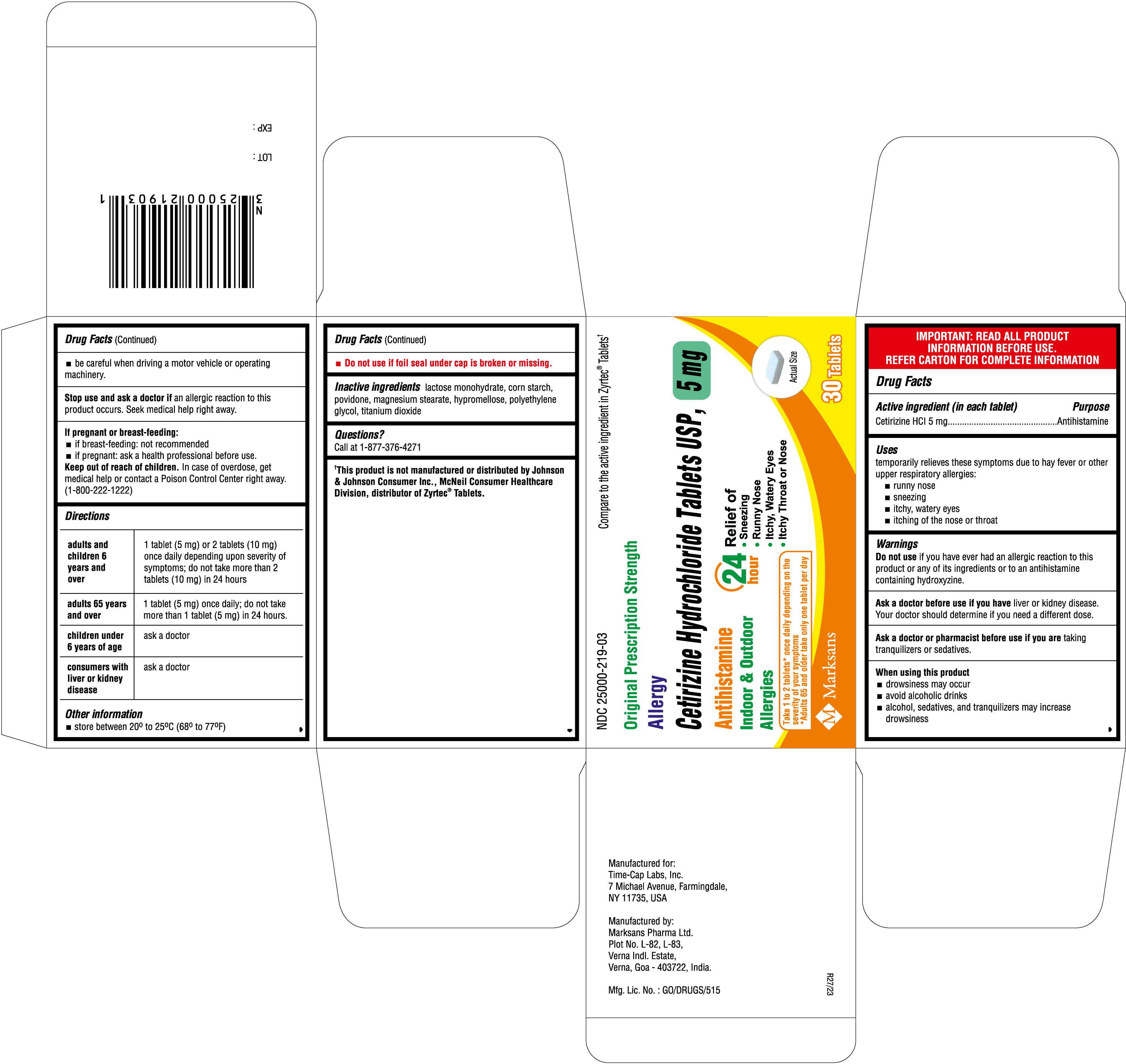 DRUG LABEL: Cetirizine Hydrochloride Tablets, 5 mg
NDC: 25000-219 | Form: TABLET
Manufacturer: MARKSANS PHARMA LIMITED
Category: otc | Type: Human OTC Drug Label
Date: 20250731

ACTIVE INGREDIENTS: CETIRIZINE HYDROCHLORIDE 5 mg/1 1
INACTIVE INGREDIENTS: LACTOSE MONOHYDRATE; STARCH, CORN; POVIDONE K30; MAGNESIUM STEARATE; HYPROMELLOSE, UNSPECIFIED; POLYETHYLENE GLYCOL, UNSPECIFIED; TITANIUM DIOXIDE

Allergy Relief
Cetirizine Hydrochloride Tablets USP, 5 mg and 10 mg

Active ingredient (in each tablet)

For 5 mg:

Cetirizine HCl USP 5 mg

For 10 mg:

Cetirizine HCl USP 10 mg

For 10 mg (Oval Shape):

Cetirizine HCl USP 10 mg

Purpose

Antihistamine

Uses

temporarily relieves these symptoms due to hay fever or other upper respiratory allergies:

- runny nose
- sneezing
- itchy, watery eyes
- itching of the nose or throat

Warnings

Do not use if you have ever had an allergic reaction to this product or any of its ingredients or to an antihistamine containing hydroxyzine.

Ask a doctor before use if you have liver or kidney disease. Your doctor should determine if you need a different dose.

Ask a doctor or pharmacist before use if you are taking tranquilizers or sedatives.

When using this product

- drowsiness may occur
- avoid alcoholic drinks
- alcohol, sedatives, and tranquilizers may increase drowsiness
- be careful when driving a motor vehicle or operating machinery

Stop use and ask a doctor if an allergic reaction to this product occurs. Seek medical help right away.

If pregnant or breast-feeding

- if breast-feeding: not recommended
- if pregnant: ask a health professional before use.

Keep out of reach of children.

In case of overdose, get medical help or contact a Poison Control Center right away. (1-800-222-1222)

Directions

For 5 mg:

adults and children 6 years and over | 1 tablet (5 mg) or 2 tablets (10 mg) once daily depending upon severity of symptoms; do not take more than 2 tablets (10 mg) in 24 hours
adults 65 years and over | 1 tablet (5 mg) once daily; do not take more than 1 tablet (5 mg) in 24 hours.
children under 6 years of age | ask a doctor
consumers with liver or kidney disease | ask a doctor

For 10 mg:

adults and children 6 years and over | one 10 mg tablet once daily; do not take more than one 10 mg tablet in 24 hours. A 5 mg product may be appropriate for less severe symptoms.
adults 65 years and over | ask a doctor
children under 6 years of age | ask a doctor
consumers with liver or kidney disease | ask a doctor

Other information

•store between 20° to 25°C (68° to 77°F)
•do not use if foil seal under cap is broken or missing

Inactive ingredients

corn starch, hypromellose, lactose monohydrate, magnesium stearate, polyethylene glycol, povidone, titanium dioxide

Questions or comments? Call 1-877-376-4271
(weekdays 9 AM to 5 PM)

PRINCIPAL DISPLAY PANEL

NDC 25000-219-03
Cetirizine Hydrochloride Tablets USP, 5 mg
30s count bottle label

NDC 25000-219-03
Cetirizine Hydrochloride Tablets USP, 5 mg
30s count carton label

NDC 25000-219-08
Cetirizine Hydrochloride Tablets USP, 5 mg
100s count bottle label

NDC 25000-219-08
Cetirizine Hydrochloride Tablets USP, 5 mg
100s count carton label

NDC 25000-219-14
Cetirizine Hydrochloride Tablets USP, 5 mg
1000s count bottle label

NDC 25000-220-03
Cetirizine Hydrochloride Tablets USP, 10 mg

30s count bottle label

NDC 25000-220-03
Cetirizine Hydrochloride Tablets USP, 10 mg

30s count carton label

NDC 25000-220-08
Cetirizine Hydrochloride Tablets USP, 10 mg
100s count bottle label

NDC 25000-220-08
Cetirizine Hydrochloride Tablets USP, 10 mg

100s count carton label

NDC 25000-220-14
Cetirizine Hydrochloride Tablets USP, 10 mg
1000s count bottle label

NDC 25000-220-78
Cetirizine Hydrochloride Tablets USP, 10 mg

7s count carton label

NDC 25000-220-81
Cetirizine Hydrochloride Tablets USP, 10 mg

14s count carton label

NDC 25000-160-81
Cetirizine Hydrochloride Tablets USP, 10 mg (Oval Shape)

14s count carton label

NDC 25000-160-03
Cetirizine Hydrochloride Tablets USP, 10 mg (Oval Shape)

30s count carton label

NDC 25000-160-03 (Oval Shape)
Cetirizine Hydrochloride Tablets USP, 10 mg

30s count bottle label

NDC 25000-160-14
Cetirizine Hydrochloride Tablets USP, 10 mg (Oval Shape)

1000s count bottle label